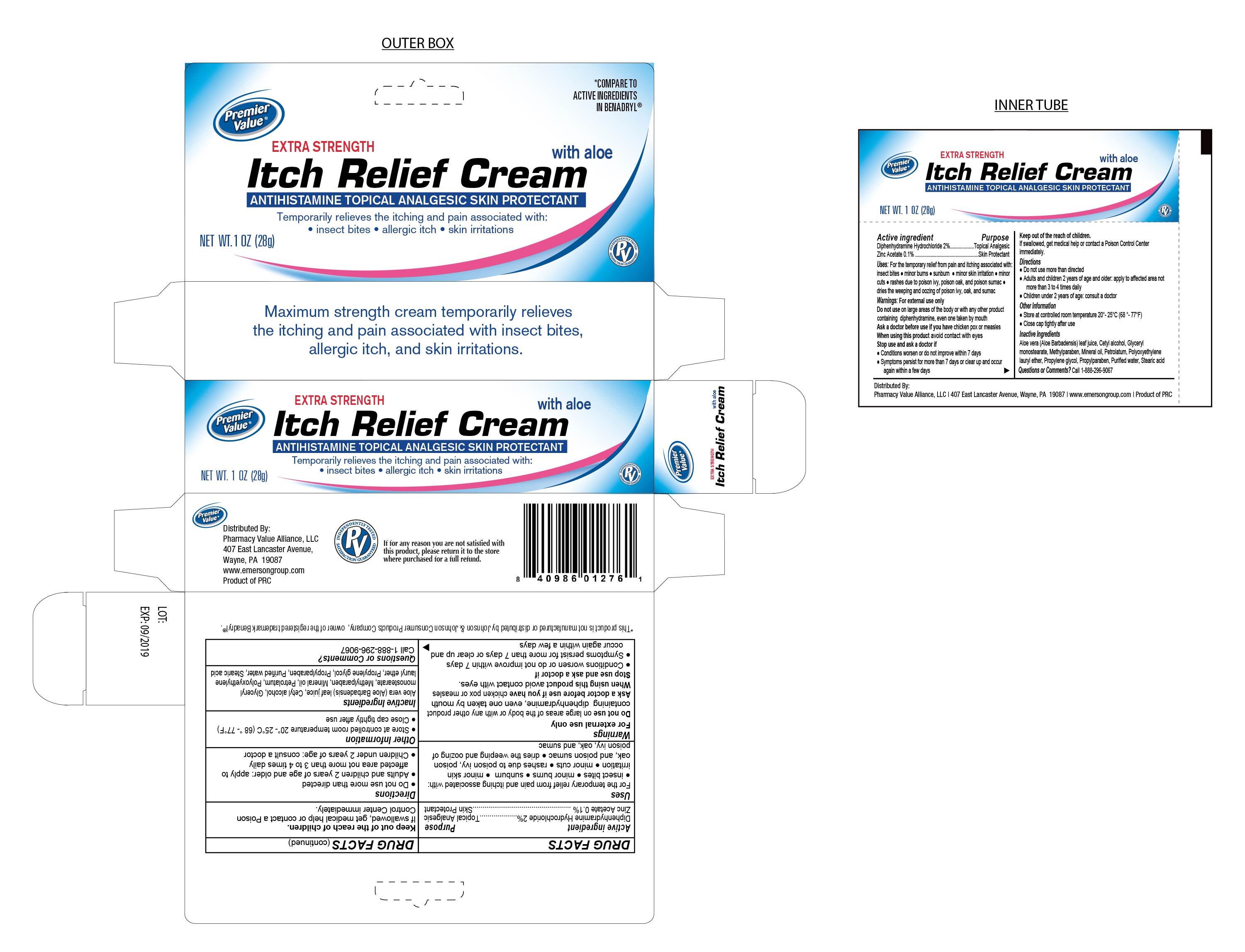 DRUG LABEL: Itch Relief Cream
NDC: 68016-163 | Form: CREAM
Manufacturer: Pharmacy Value Alliance LLC
Category: otc | Type: HUMAN OTC DRUG LABEL
Date: 20241220

ACTIVE INGREDIENTS: DIPHENHYDRAMINE HYDROCHLORIDE 2 g/100 g; ZINC ACETATE 0.1 g/100 g
INACTIVE INGREDIENTS: METHYLPARABEN; GLYCERYL MONOSTEARATE; PETROLATUM; LAURETH-23; WATER; MINERAL OIL; PROPYLPARABEN; STEARYL ALCOHOL; PROPYLENE GLYCOL; STEARIC ACID; CETOSTEARYL ALCOHOL

Itch Relief Cream

Active Ingredient

Diphenhydramine Hydrochloride 2%

Purpose

Topical Analgesic

Active Ingredient

Zinc Acetate 0.1%

Purpose

Skin Protectant

Uses

For the temporary relief from pain and itcing assciated with:

- insect bites
- minor burns
- sunburn
- minor skin irritation
- minor cuts
- rashes due to poison ivy, poison oak, and poison sumac
- dries weeping and oozing of poison ivy, oak, and sumac

Warnings

For External Use only

Do not use on large areas of the body or with any other product containing diphenhydramine, even one taken by mouth

Ask a doctor before use if you have chicken pox or measles

When using this product avoid contact with eyes.

Stop Use and ask a doctor if

- Conditions worsen or do not improve within 7 days
- Symptoms persist for more than 7 days or clear up and occur again within a few days

Keep out of the reach of children.

If swallowed, get medical help or contact Poison Control Center immediately

Directions

- Do not use more than directed
- Adults and children 2 years of age and older: apply to affected area not more than 3 to 4 times daily
- Children under 2 years of age: consult a doctor

Other Information

- Store at controlled room temperature 20°-25°C (68°-77°F)
- Close cap tightly after use

Inactive Ingredients

Aloe Vera (Aloe Barbadensis), leaf juice, Cetyl alcohol, Glyceryl monostearate, Methylparaben, Mineral Pil, Petrolatum, Polyoxyethylene, lauryl ether, Propylene glycol, Propylparaben, Purified Water, Stearic acid

Itch Relief Cream Antihistamine Topical Analgesic Skin Protectant

Temporarily relieves the itching and pain associated with:

- insect bites
- allergic itch
- skin irritations

Distributed By:

Pharmacy Value Alliance, LLC.

407 East Lancaster Avenue

Wayne, PA. 19087

www.emersongroup.com

Product of PRC